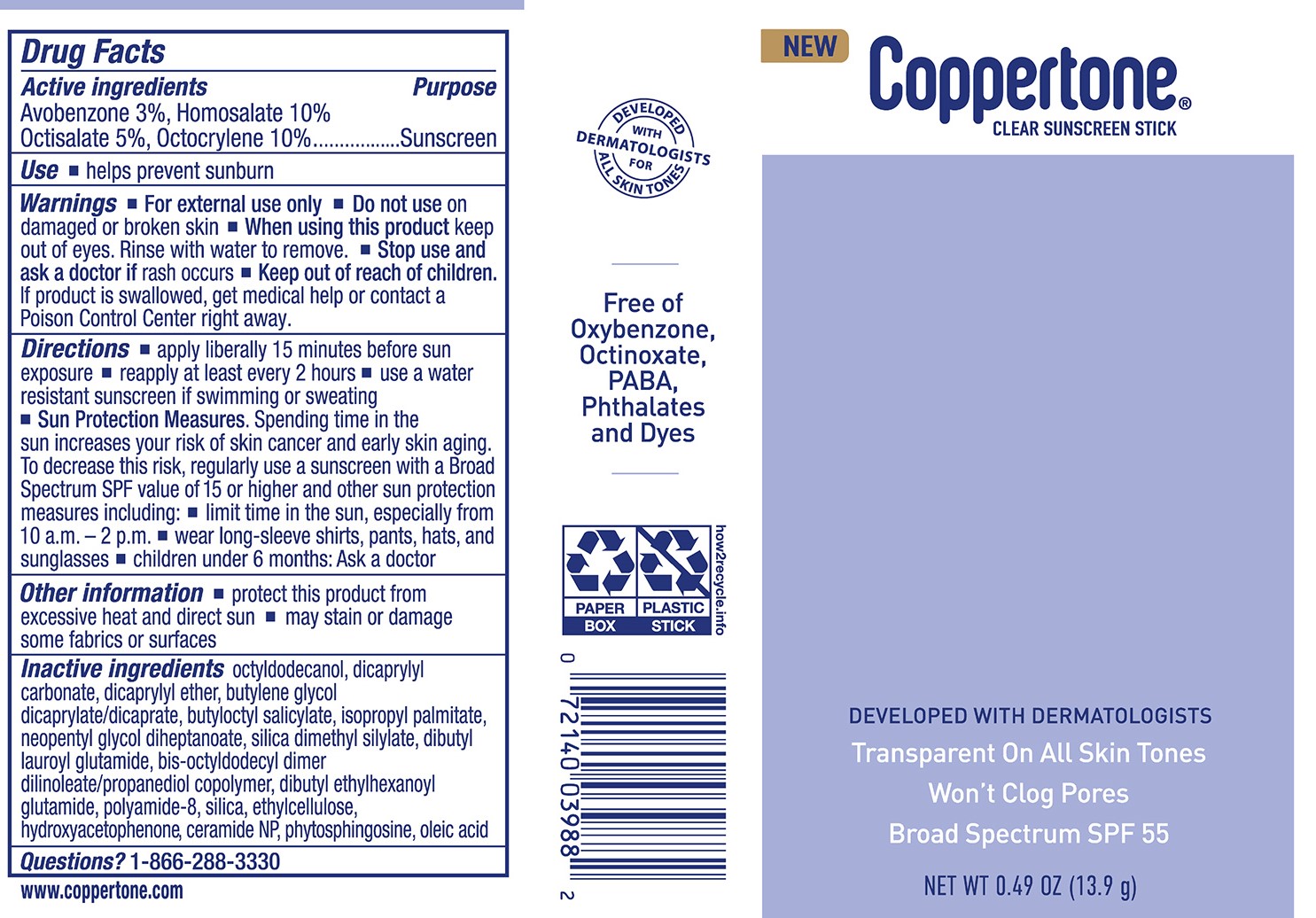 DRUG LABEL: Coppertone Every Tone Invisible Clear Sunscreen Stick SPF 55
NDC: 66800-8003 | Form: STICK
Manufacturer: Beiersdorf Inc
Category: otc | Type: HUMAN OTC DRUG LABEL
Date: 20251231

ACTIVE INGREDIENTS: OCTISALATE 5 g/100 g; AVOBENZONE 3 g/100 g; OCTOCRYLENE 10 g/100 g; HOMOSALATE 10 g/100 g
INACTIVE INGREDIENTS: DICAPRYLYL CARBONATE; BUTYLOCTYL SALICYLATE; CALCIUM SILICATE; ETHYLCELLULOSES; OCTYLDODECANOL; ISOPROPYL PALMITATE; SILICA DIMETHYL SILYLATE; BIS-OCTYLDODECYL DIMER DILINOLEATE/PROPANEDIOL COPOLYMER; POLYAMIDE-8 (4500 MW); HYDROXYACETOPHENONE; PHYTOSPHINGOSINE; OLEIC ACID; DIBUTYL LAUROYL GLUTAMIDE; BUTYLENE GLYCOL DICAPRYLATE/DICAPRATE; CERAMIDE NP; DIBUTYL ETHYLHEXANOYL GLUTAMIDE; DICAPRYLYL ETHER; NEOPENTYL GLYCOL DIHEPTANOATE

Coppertone Every Tone Invisible Stick Sunscreen SPF 55

Active ingredients

Avobenzone 3%, Homosalate 10%,
Octisalate 5%, Octocrylene 10%

Purpose

Sunscreen

Uses

■ helps prevent sunburn
■ if used as directed with other sun protection measures (see Directions),
decreases the risk of skin cancer and early skin aging caused by the sun

WARNINGS

For external use only

Do not useon damaged or broken skin

WHEN USING

When using this productkeep out of eyes. Rinse with water to remove.

Stop use and ask a doctor ifrash occurs

Keep out of reach of children.If product is swallowed, get medical help or
contact a Poison Control Center right away.

Directions

■ apply liberally 15 minutes before sun exposure
■ reapply at least every 2 hours
■ use a water resistant sunscreen if swimming or sweating
■ Sun Protection Measures.Spending time in the sun increases your risk of skin
cancer and early skin aging. To decrease this risk, regularly use a sunscreen
with a Broad Spectrum SPF value of 15 or higher and other sun protection
measures including:
■ limit time in the sun, especially from 10 a.m. – 2 p.m.
■ wear long-sleeve shirts, pants, hats, and sunglasses
■ children under 6 months: Ask a doctor

Other information

■ protect this product from excessive heat and direct sun
■ may stain or damage some fabrics or surfaces

Inactive ingredients

octyldodecanol, dicaprylyl carbonate, dicaprylyl ether, butylene glycol dicaprylate/dicaprate, butyloctyl salicylate, isopropyl
palmitate, neopentyl glycol diheptanoate, silica dimethyl silylate, dibutyl lauroyl glutamide, bis-octyldodecyl dimer dilinoleate/propanediol copolymer, dibutyl ethylhexanoyl glutamide, polyamide-8, silica, ethylcellulose, hydroxyacetophenone, ceramide NP, phytosphingosine, oleic acid

Questions?

1-866-288-3330

PACKAGE LABEL

NEW

Coppertone®Clear Sunscreen Stick

Developed with Dermatologists

Transparent on all skin tones

Won't clog pores

Broad Spectrum SPF 55

NET WT 0.49 OZ (13.9 g)